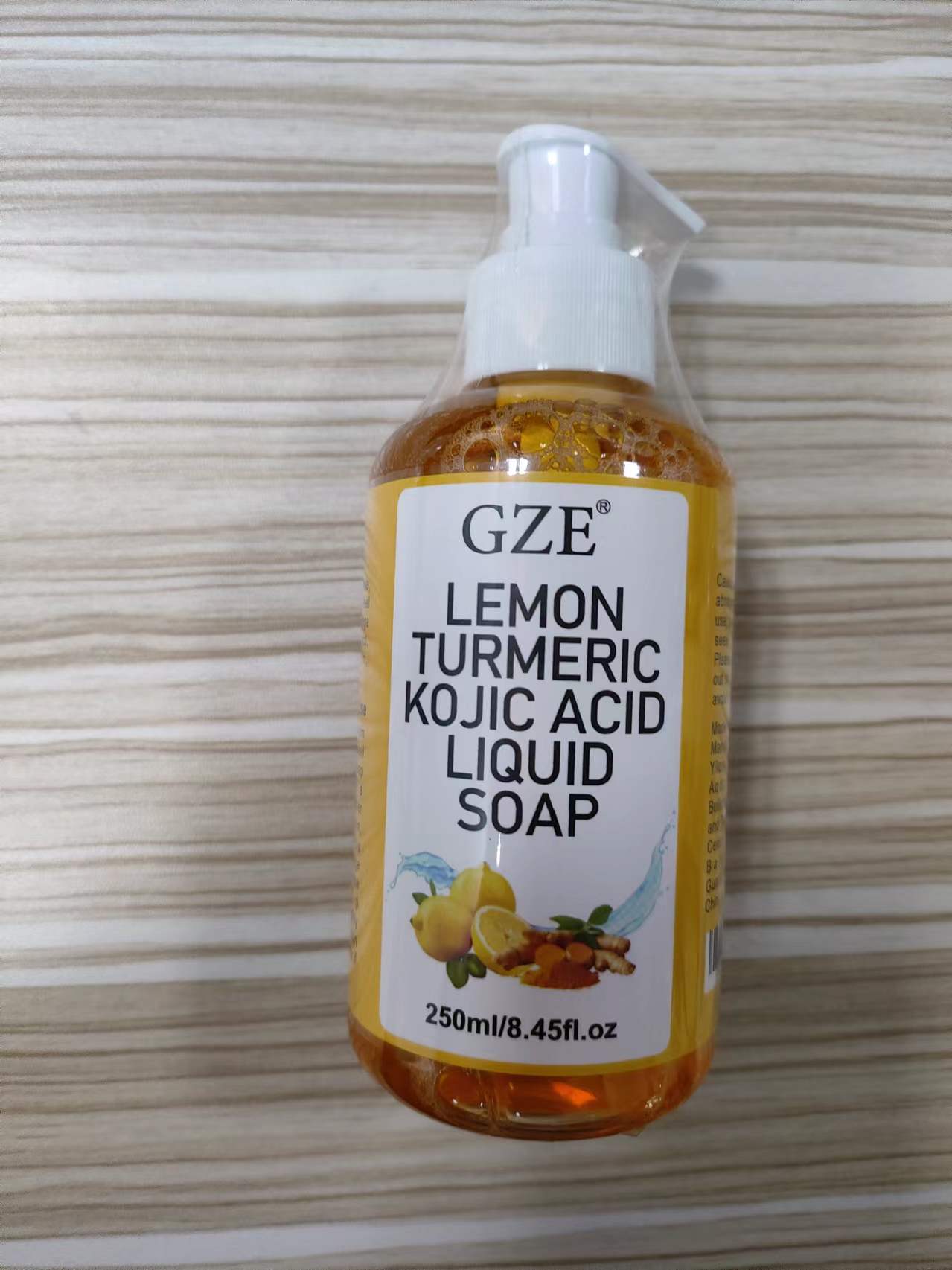 DRUG LABEL: GZE Lemon Turmeric Kojic Acid LiquidSoap
NDC: 74458-404 | Form: LIQUID
Manufacturer: Guangzhou Yilong Cosmetics Co., Ltd
Category: otc | Type: HUMAN OTC DRUG LABEL
Date: 20241109

ACTIVE INGREDIENTS: KOJIC ACID 0.6 g/100 mL
INACTIVE INGREDIENTS: CURCUMA LONGA (TURMERIC) ROOT EXTRACT; GLYCERIN; SODIUM HYDROXIDE; CITRUS LIMON (LEMON) PEEL EXTRACT; WATER

GZE LEMON TURMERIC KOJIC ACID LIQUID SOAP

ACTIVE INGREDIENT

Kojic Acid

INACTIVE INGREDIENT

Water, Sodium Hydroxide, Citrus Limon (Lemon) Peel Extract, Curcuma Longa (Turmeric) Root Extract, Glycerin, Fragrance.

PURPOSE

Exfoliating.

INDICATIONS AND USAGE

Wet your skin with warm water. Apply a small amount of the liquid soap to your hands or a washcloth. Gently lather the soap on your skin, focusing on areas you want to brighten. Massage for 1-2 minutes to allow the ingredients to p enetrate.Rinse tho roughly with water. Pat your skin dry and apply moisturizer if needed.

WARNINGS

For external use only.

Stop use and ask a doctor if rash occurs.

Do not use on damaged or broken skin.

When using this product keep out of eyes. Rinse with water to remove.

Keep out of reach of children. If swallowed, get medical help or contact a Poison Control Center right away.

DOSAGE AND ADMINISTRATION

Wet your skin with warm water. Apply a small amount of the liquid soap to your hands or a washcloth. Gently lather the soap on your skin, focusing on areas you want to brighten. Massage for 1-2 minutes to allow the ingredients to p enetrate.Rinse tho roughly with water. Pat your skin dry and apply moisturizer if needed.